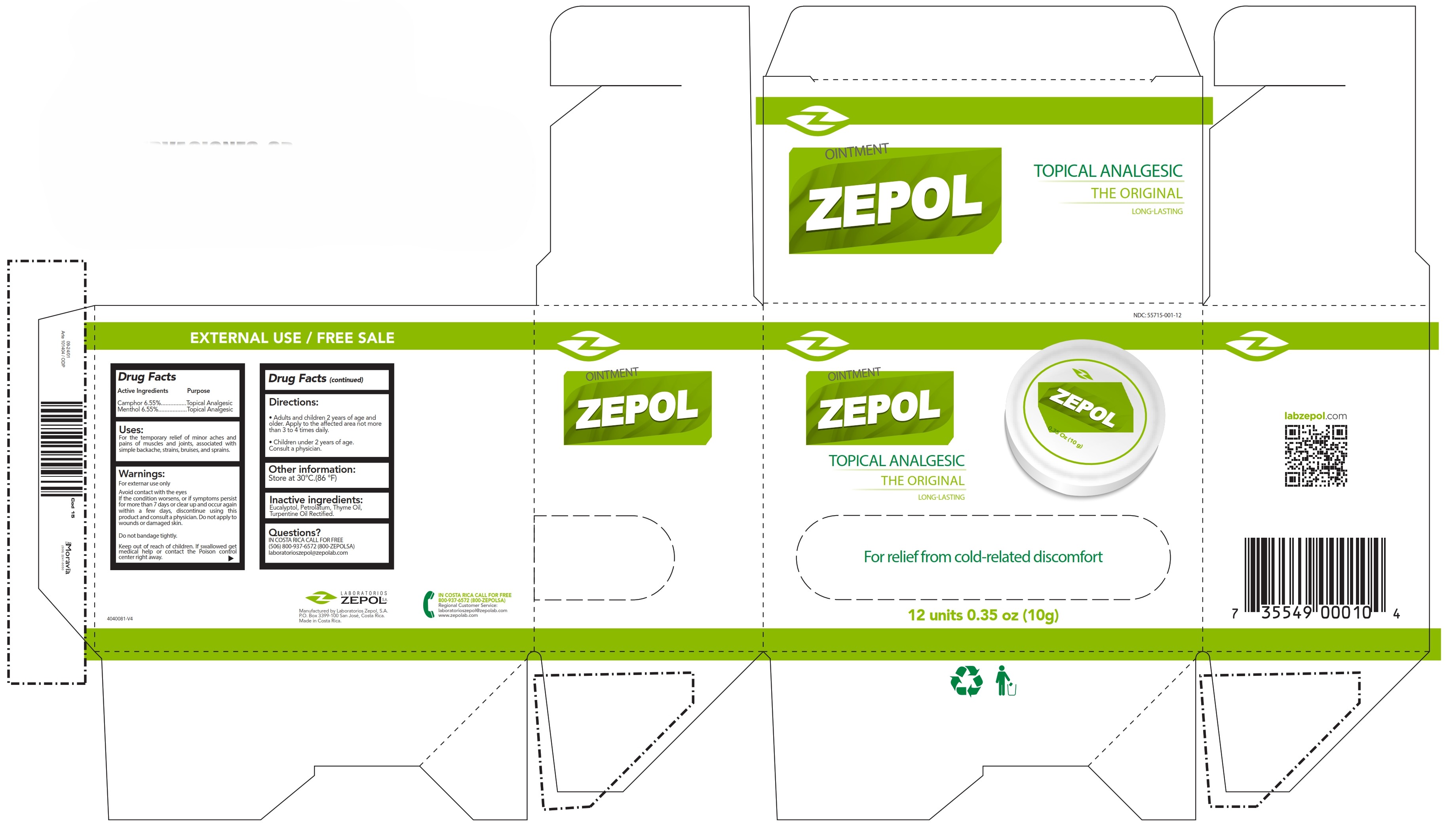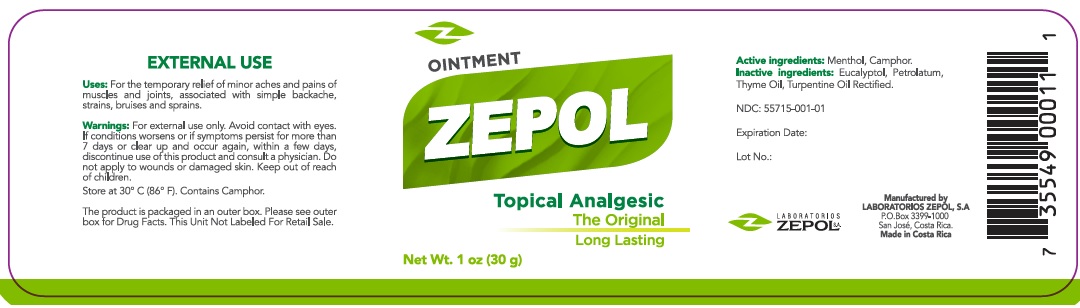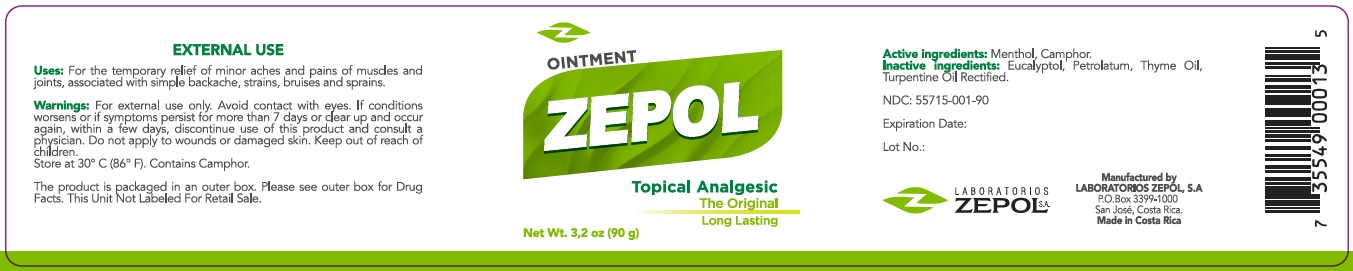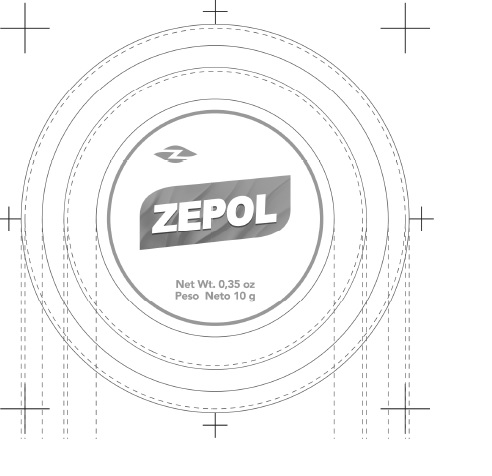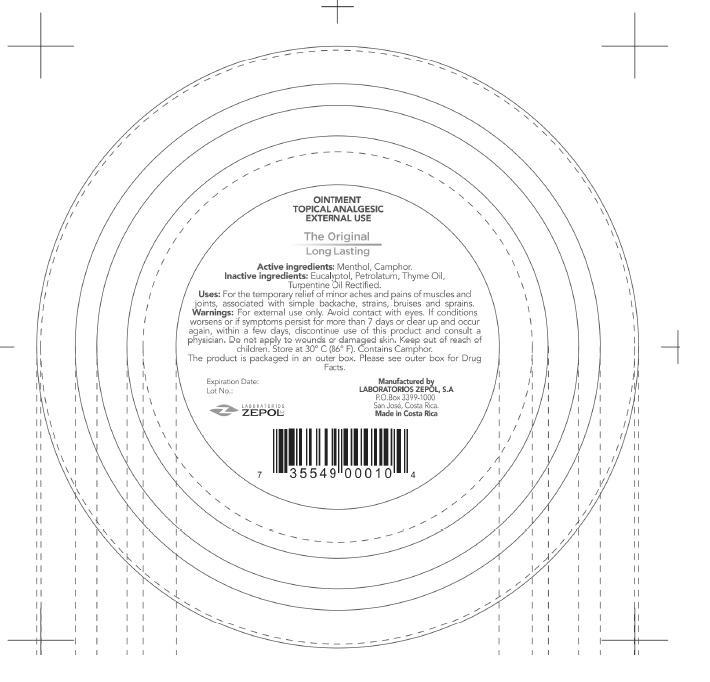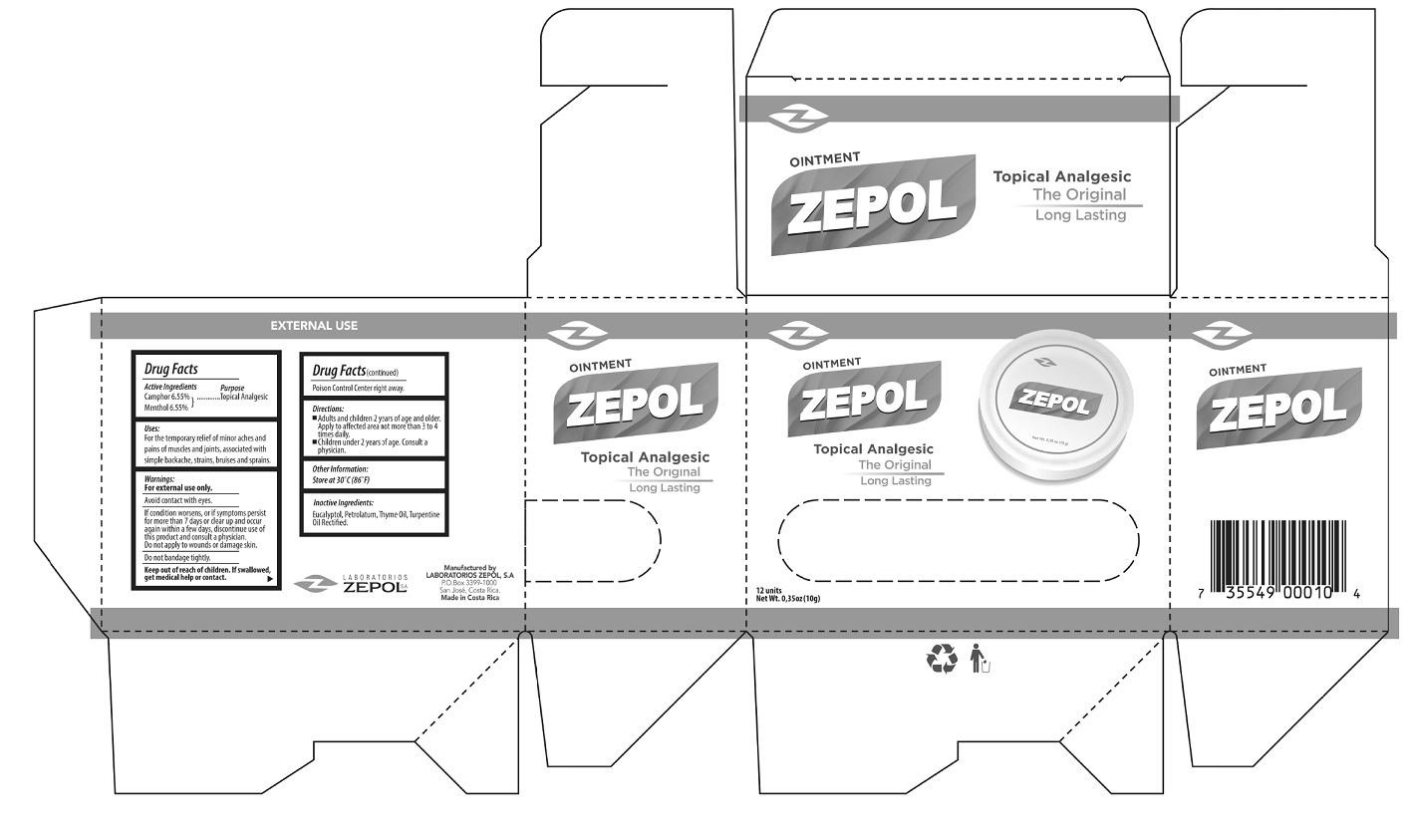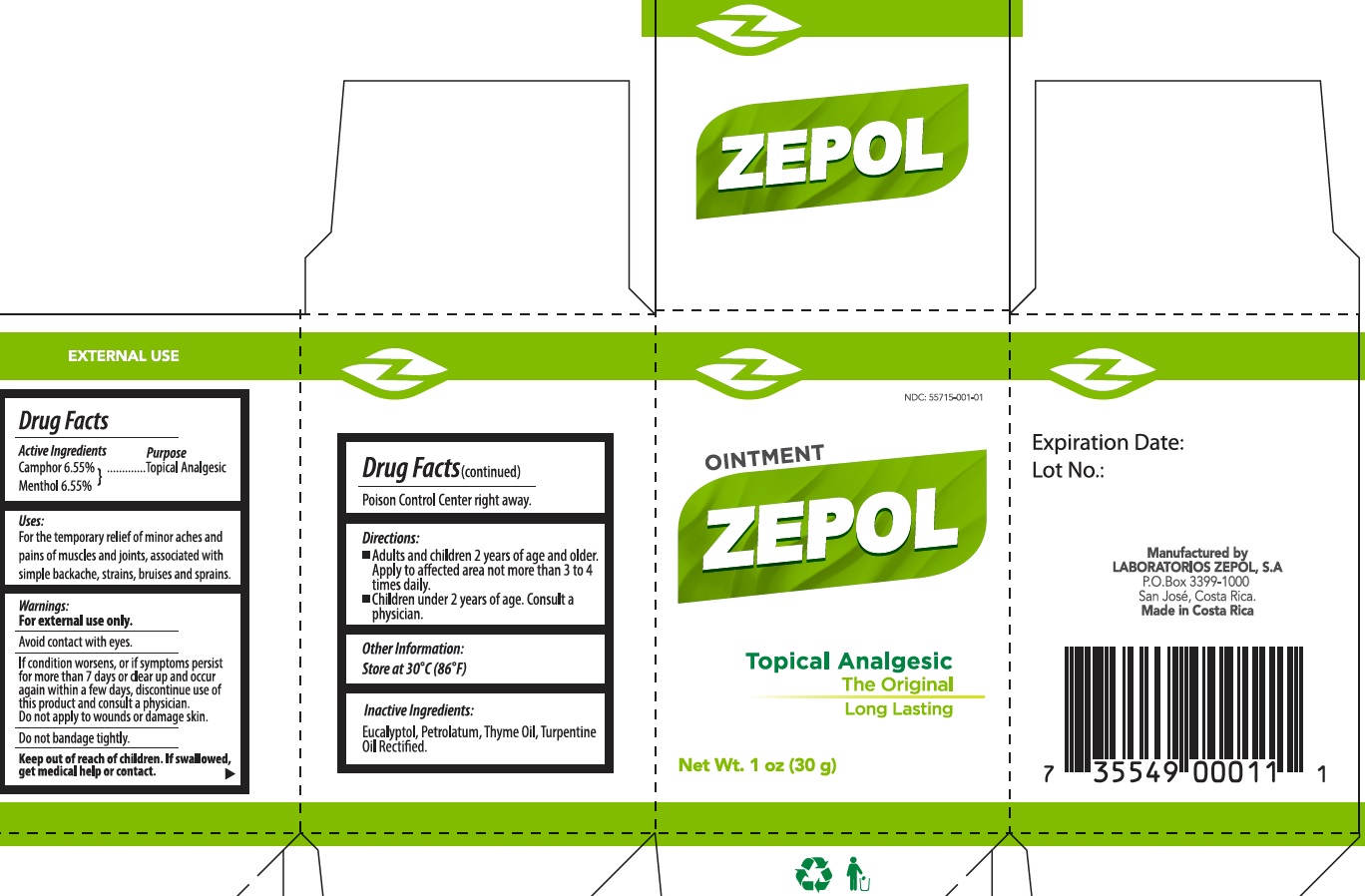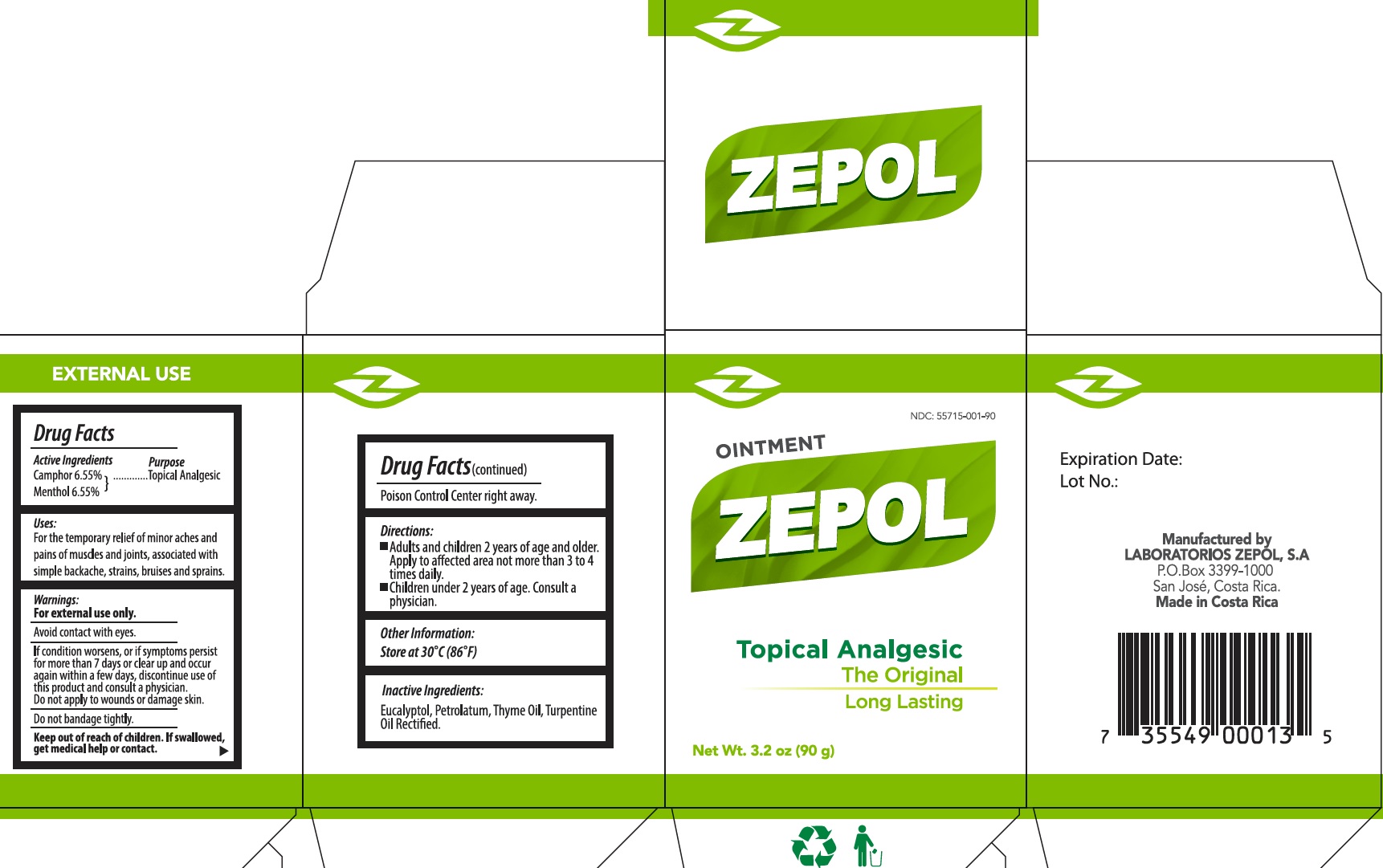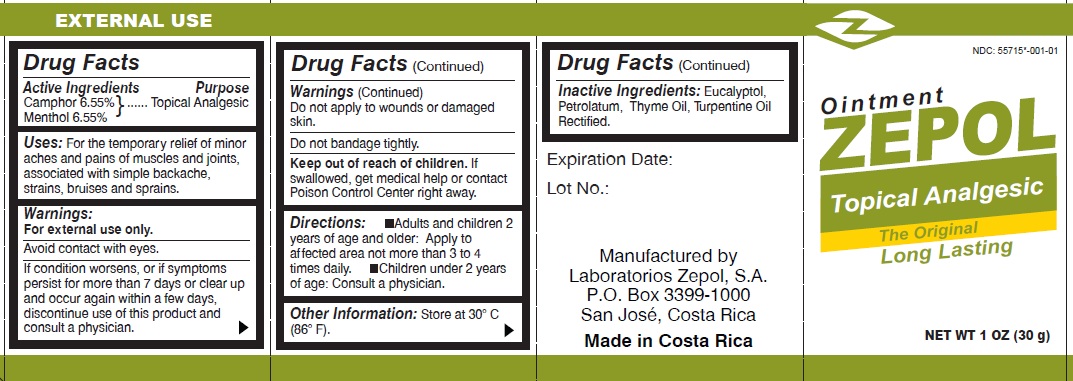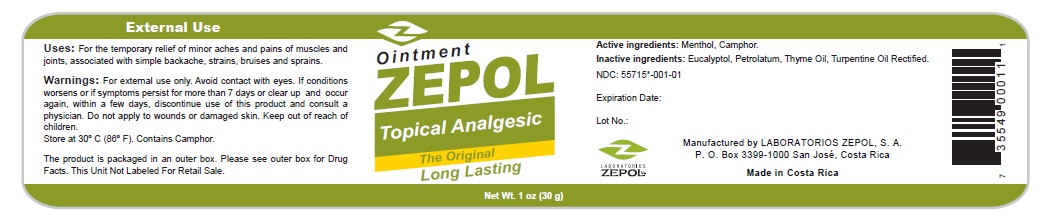 DRUG LABEL: Zepol Topical Analgesic
NDC: 55715-001 | Form: OINTMENT
Manufacturer: Laboratorios Zepol S.A.
Category: otc | Type: HUMAN OTC DRUG LABEL
Date: 20250409

ACTIVE INGREDIENTS: CAMPHOR (SYNTHETIC) 6.55 g/100 g; MENTHOL 6.55 g/100 g
INACTIVE INGREDIENTS: EUCALYPTOL; PETROLATUM; TURPENTINE; THYME OIL

Zepol Topical Analgesic Ointment

Active Ingredients

Camphor 6.55%
Menthol 6.55%

Purpose

Topical Analgesic

Uses

For the temporary relief of minor aches and pains of muscles and joints, associated with simple backache, strains, bruises and sprains.

Warnings

For external use only.
Avoid contact with eyes.
If condition worsens, or if symptoms persist for more than 7 days or clear up and occur again within a few days, discontinue use of this product and consult a physician.

Do not apply

to wounds or damaged skin.
Do not bandage tightly.

Keep out of reach of children.

If swallowed, get medical help or contact Poison Control Center right away.

Directions:

-Adults and children 2 years of age and older: Apply to affected area not more than 3 to 4 times daily. -Children under 2 years of age: Consult a physician.

Other information

Store at 30 degrees C (86 degrees F).

Inactive Ingredients

Eucalyptol, Petrolatum, Thyme Oil, Turpentine Oil Rectified.

Zepol Topical Analgesic Ointment Box

NDC 55715-001-12

Ointment ZEPOL

Topical Analgesic

The original

Long-Lasting

For relief from cold-related discomfort412 units 0.35oz (10g)

Manufactured by Laboratorios Zepol, S.A.

P.O. Box 3399-100 San José, Costa Rica.

Made in Costa Rica.

IN COSTA RICA CALL FOR FREE

800-937-6572 (800-ZEPOLSA)

Regional Customer Service:

laboratorioszepol@zepolab.com

www.zepolab.com